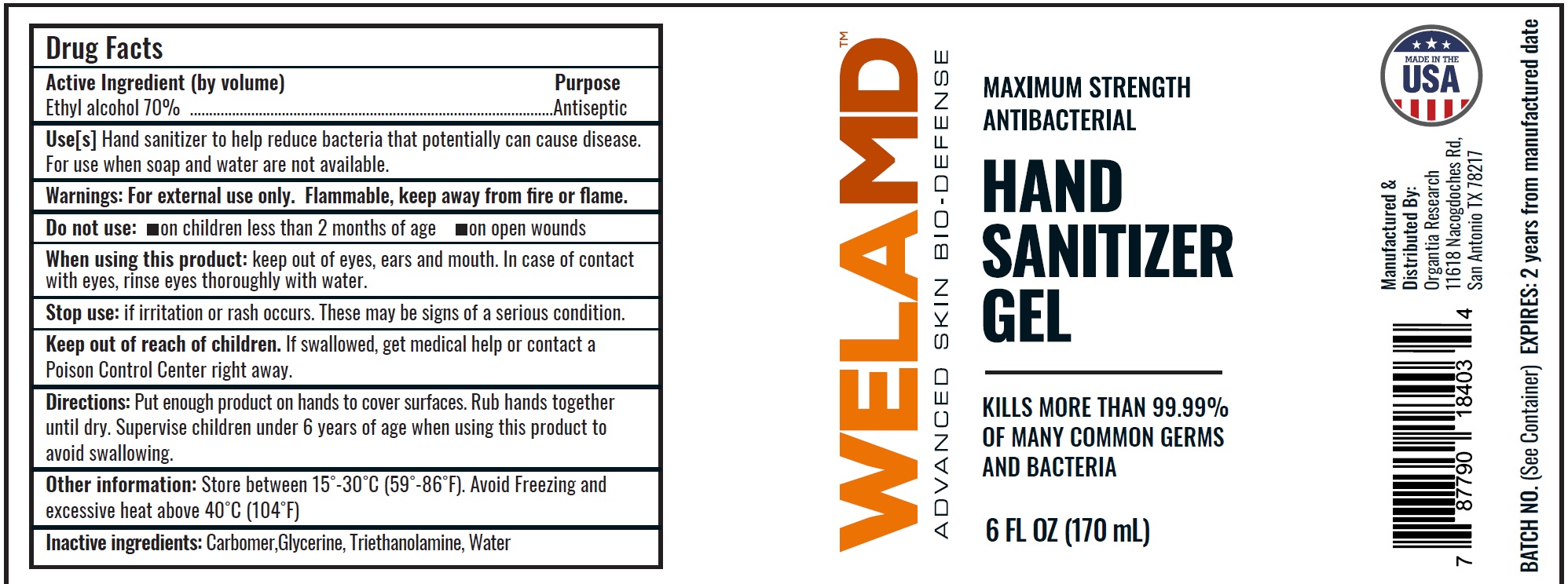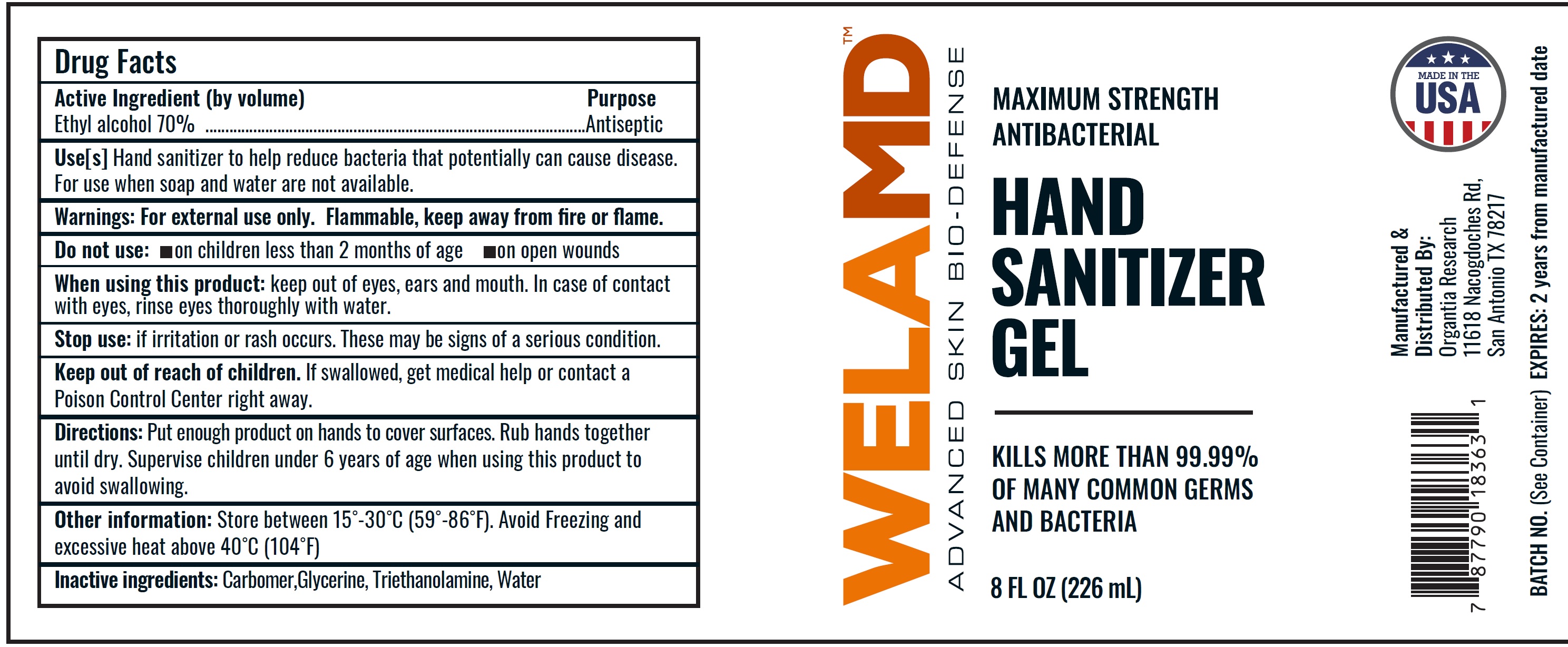 DRUG LABEL: WELAMD Maximum Strength Antibacterial Hand Sanitizer
NDC: 80595-001 | Form: GEL
Manufacturer: AVP Labs and Investment Group LLC
Category: otc | Type: HUMAN OTC DRUG LABEL
Date: 20200928

ACTIVE INGREDIENTS: ALCOHOL 0.7 mL/1 mL
INACTIVE INGREDIENTS: CARBOMER HOMOPOLYMER, UNSPECIFIED TYPE; GLYCERIN; TROLAMINE; WATER

WELAMD Maximum Strength Antibacterial Hand Sanitizer

Active Ingredient (by volume)

Ethyl alcohol 70%

Purpose

Antiseptic

Use[s]

Hand sanitizer to help reduce bacteria that potentially can cause disease. For use when soap and water are not available.

Warnings:

For external use only. Flammable, keep away from fire or flame.

Do not use:

- on children less than 2 months of age
- on open wounds

When using this product:

keep out of eyes, ears and mouth. In case of contact with eyes, rinse eyes thoroughly with water.

Stop use:

if irritation or rash occurs. These may be signs of a serious condition.

Keep out of reach of children.

If swallowed, get medical help or contact a Poison Control Center right away.

Directions:

Put enough product on hands to cover surfaces. Rub hands together until dry. Supervise children under 6 years of age when using this product to
avoid swallowing.

Other information:

Store between 15˚-30˚C (59˚-86˚F). Avoid Freezing and excessive heat above 40˚C (104˚F)

Inactive ingredients:

Carbomer,Glycerine, Triethanolamine, Water